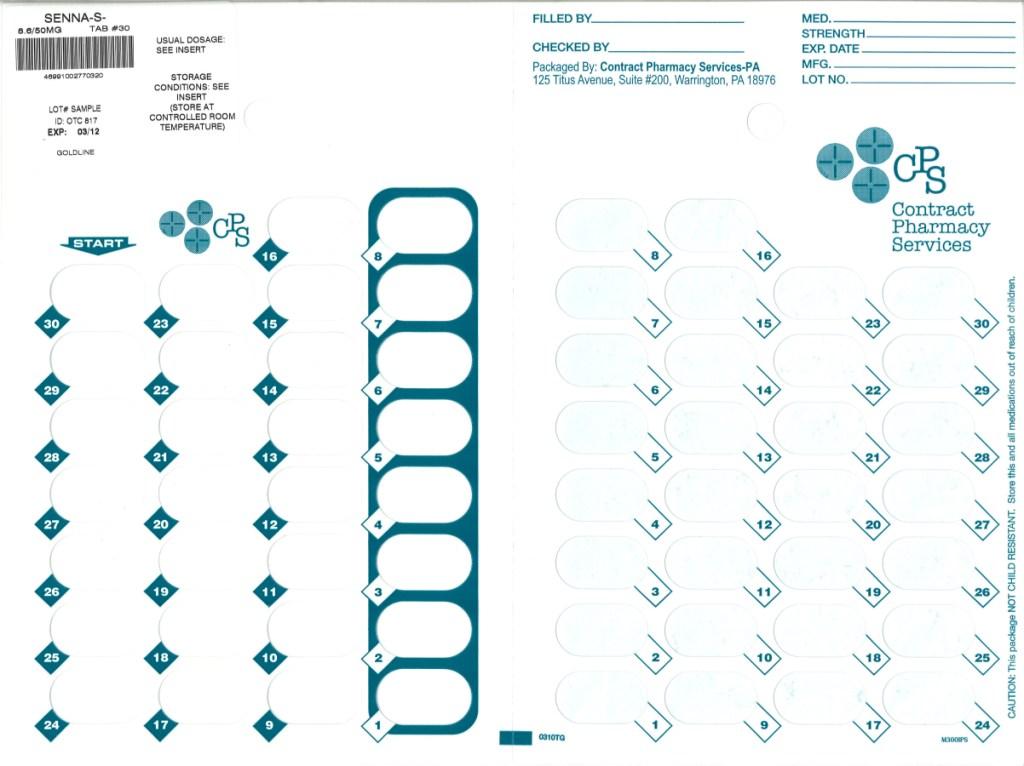 DRUG LABEL: Senna-S
NDC: 67046-670 | Form: TABLET, FILM COATED
Manufacturer: Contract Pharmacy Services-PA
Category: otc | Type: HUMAN OTC DRUG LABEL
Date: 20100730

ACTIVE INGREDIENTS: DOCUSATE SODIUM 50 mg/1 1; SENNOSIDES 8.6 mg/1 1
INACTIVE INGREDIENTS: CARNAUBA WAX; SILICON DIOXIDE; CROSCARMELLOSE SODIUM; DIBASIC CALCIUM PHOSPHATE DIHYDRATE; D&C YELLOW NO. 10; FD&C YELLOW NO. 6; HYPROMELLOSE; MAGNESIUM STEARATE; CELLULOSE, MICROCRYSTALLINE; POLYETHYLENE GLYCOL; SODIUM BENZOATE; STEARIC ACID; STARCH, TAPIOCA; TARTARIC ACID; TITANIUM DIOXIDE; ALUMINUM OXIDE

SENNA-S Tablets

ACTIVE INGREDIENT (IN EACH TABLET)

Docusate sodium 50 mg

Sennosides 8.6 mg

PURPOSE

Stool softener & Stimulant laxative

USES

- relieves occasional constipation (irregularity)
- generally causes a bowel movement in 6 to 12 hours

WARNINGS

Do not use

- this product if you are presently taking mineral oil, unless directed by a doctor
- laxative products for more than 1 week unless directed by a doctor

Ask a doctor before use if you have

- stomach pain
- nausea
- vomiting
- a sudden change in bowel habits that persists over 2 weeks

Stop use and ask a doctor if you have

- have rectal bleeding
- fail to have a bowel movement after the use of a laxative

These could be signs of a serious condition

If pregnant or breast-feeding,

ask a health professional before use.

Keep out of reach of children.

In case of overdose, get medical help or contact a Poison Control Center right away.

DIRECTIONS

- take preferably at bedtime or as directed by a doctor
- if you do not have a comfortable bowel movement by the second day, increase dose by one tablet (do not exceed maximum dosage); or decrease dose until you are comfortable
-
  age | starting dose | maximum dose
  adults and children 12 years and over | 2 tablets once a day | 4 tablets twice a day
  children 6 to under 12 years | 1 tablet once a day | 2 tablets twice a day
  children 2 to under 6 years | 1/2 tablet once a day | 1 tablet twice a day
  children under 2 years | ask a doctor | ask a doctor

OTHER INFORMATION

- each tablet contains: calcium 20 mg, sodium 6 mg (LOW SODIUM)
- TAMPER-EVIDENT: Do not use this product if foil seal on back of blister is cut, torn, broken or missing
- store at 25°C (77°F) excursions permitted between 15°-30°C (59°-86°F)

INACTIVE INGREDIENTS

carnauba wax, colloidal silicon dioxide, croscarmellose sodium, dibasic calcium phosphate dihydrate, D&C yellow #10 aluminum lake, FD&C yellow #6 aluminum lake, hypromellose, magnesium stearate, microcrystalline cellulose, polyethylene glycol, sodium benzoate, stearic acid, tapioca starch1, tartaric acid1, titanium dioxide

1 may contain these ingredients

QUESTIONS OR COMMENTS?

call 1-888-838-2872, weekdays, 8 AM-5 PM Eastern Time

Distributed by:
GOLDLINE LABORATORIES, INC.
Sellersville, PA 18960 Dist. 1999 0110REV 89
192B R1009

Repackaged by:
Contract Pharmacy Services-PA
125 Titus Ave Suite 200
Warrington, PA 18976 USA

Original--08/2010--NJW